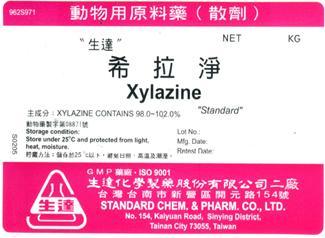 DRUG LABEL: Xylaxine
NDC: 63537-0092 | Form: POWDER
Manufacturer: Standard Chem. & Pharm. Co., Ltd.
Category: other | Type: BULK INGREDIENT
Date: 20130705

ACTIVE INGREDIENTS: XYLAZINE 1 kg/1 kg

Xylazine

PACKAGE LABEL

Xylazine